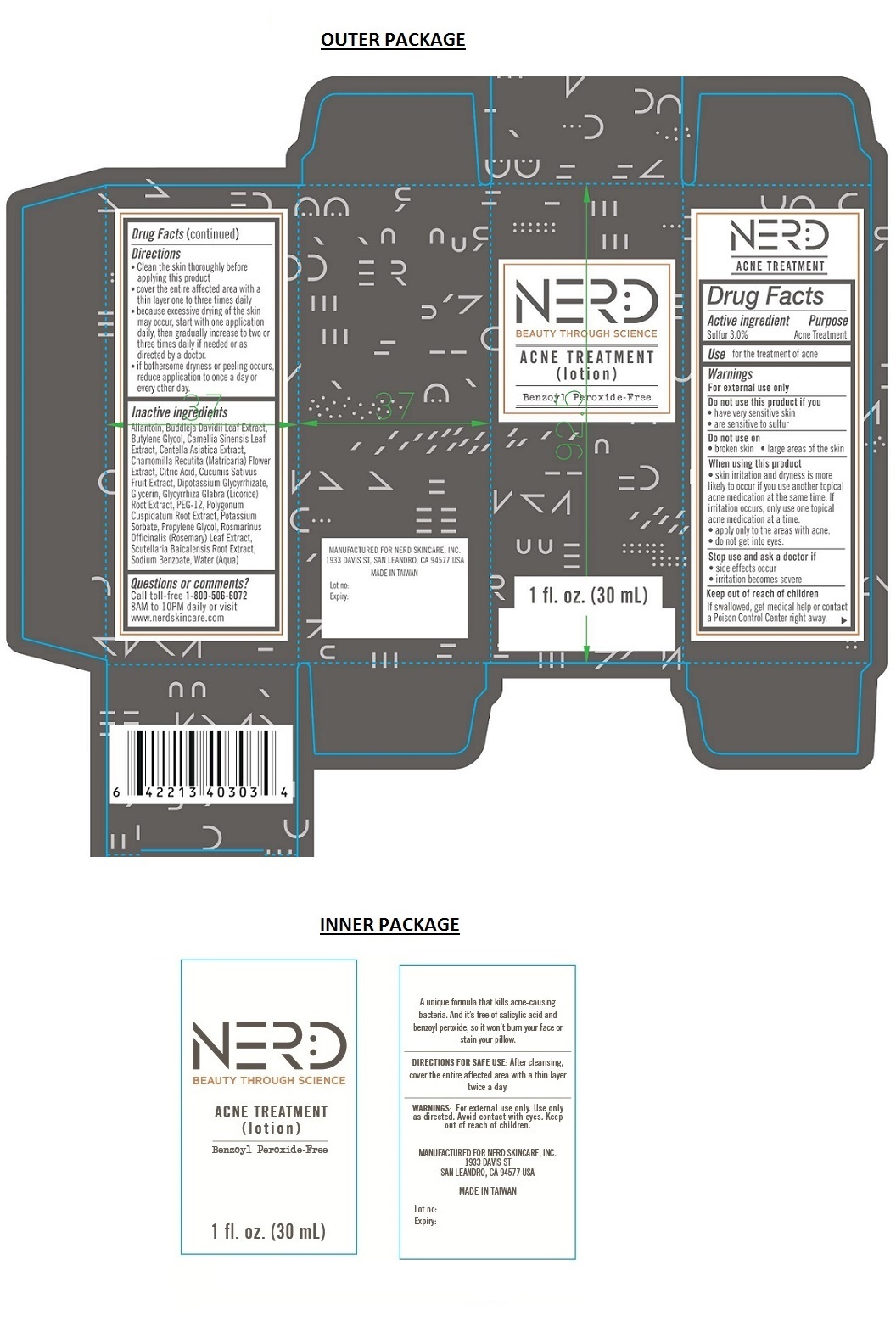 DRUG LABEL: NERD ACNE TREATMENT
NDC: 70425-101 | Form: LOTION
Manufacturer: Panco Cosmetics Corp.
Category: otc | Type: HUMAN OTC DRUG LABEL
Date: 20160114

ACTIVE INGREDIENTS: SULFUR 0.9 g/30 mL
INACTIVE INGREDIENTS: ALLANTOIN; BUDDLEJA DAVIDII LEAF; BUTYLENE GLYCOL; GREEN TEA LEAF; CENTELLA ASIATICA; CHAMOMILE; CITRIC ACID MONOHYDRATE; CUCUMBER; GLYCYRRHIZINATE DIPOTASSIUM; GLYCERIN; GLYCYRRHIZA GLABRA; POLYETHYLENE GLYCOL 600; POLYGONUM CUSPIDATUM ROOT; POTASSIUM SORBATE; PROPYLENE GLYCOL; ROSEMARY; SCUTELLARIA BAICALENSIS ROOT; SODIUM BENZOATE; WATER

NERD ACNE TREATMENT (lotion)

Active ingredient

Sulfur 3.0%

Purpose

Acne Treatment

Keep out of reach of children

If swallowed, get medical help or contact a Poison Control Center right away.

INDICATIONS AND USAGE

Use for the treatment of acne

Warnings

For external use only

Do not use this product if you

• have very sensitive skin

• are sensitive to sulfur

Do not use on

• broken skin • large areas of the skin

When using this product

• skin irritation and dryness is more likely to occur if you use another topical acne medication at the same time. If irritation occurs, only use one topical acne medication at a time.

• apply only to the areas with acne.

• do not get into eyes.

Stop use and ask a doctor if

• side effects occur

• irritation becomes severe

Directions

• Clean the skin thoroughly before applying this product
• cover the entire affected area with a thin layer one to three times daily
• because excessive drying of the skin may occur, start with one application daily, then gradually increase to two or three times daily if needed or as directed by a doctor.
• if bothersome dryness or peeling occurs, reduce application to once a day or every other day.

Inactive ingredients

Allantoin, Buddleja Davidii Leaf Extract, Butylene Glycol, Camellia Sinensis Leaf Extract, Centella Asiatica Extract, Chamomilla Recutita (Matricaria) Flower Extract, Citric Acid, Cucumis Sativus Fruit Extract, Dipotassium Glycyrrhizate, Glycerin, Glycyrrhiza Glabra (Licorice) Root Extract, PEG-12, Polygonum Cuspidatum Root Extract, Potassium Sorbate, Propylene Glycol, Rosmarinus Officinalis (Rosemary) Leaf Extract, Scutellaria Baicalensis Root Extract, Sodium Benzoate, Water (Aqua)

Questions or comments?

Call toll-free 1-800-506-6072
8AM to 10PM daily or visit
www.nerdskincare.com

A unique formula that kills acne-causing bacteria. And it's free of salicylic acid and benzoyl peroxide, so it won't burn your face or stain your pillow.

Benzoyl Peroxide- Free

MANUFACTURED FOR NERD SKINCARE, INC.
1933 DAVIS ST, SAN LEANDRO, CA 94577 USA

MADE IN TAIWAN